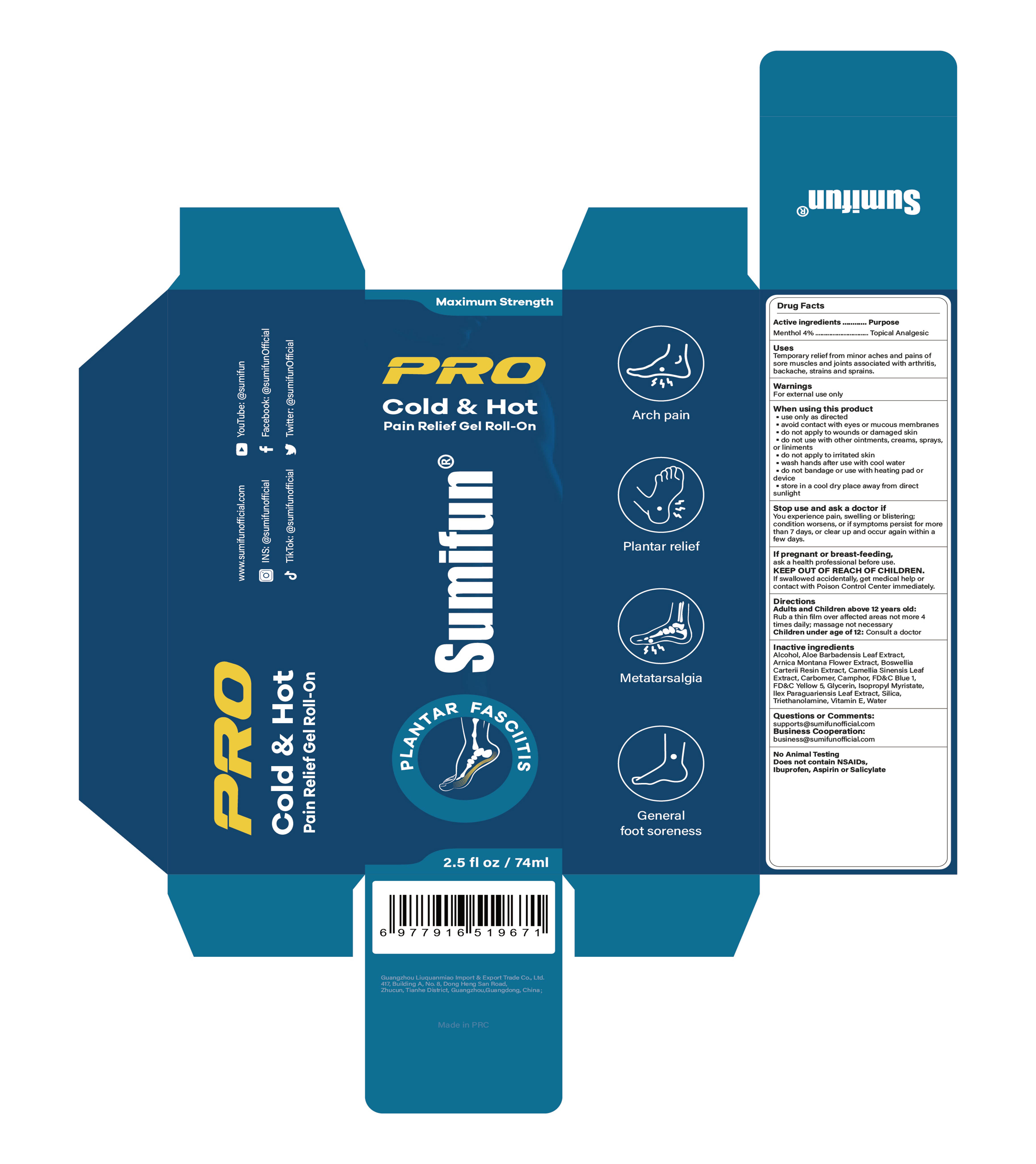 DRUG LABEL: PRO COLD  HOT Pain Relief Gel Roll-On (Plantar Fasciitis)
NDC: 84165-013 | Form: GEL
Manufacturer: Guangzhou Zhupuyou E-commerce Co., Ltd
Category: otc | Type: HUMAN OTC DRUG LABEL
Date: 20250612

ACTIVE INGREDIENTS: MENTHOL 4 g/100 mL
INACTIVE INGREDIENTS: ALCOHOL 95%; CARBOMER; TRIETHANOLAMINE; .ALPHA.-TOCOPHEROL, D-; ISOPROPYL MYRISTATE; ALOE BARBADENSIS LEAF; ARNICA MONTANA FLOWER; OLIBANUM; CAMELLIA SINENSIS LEAF; WATER; CAMPHOR (SYNTHETIC); FD&C BLUE NO. 1; GLYCERIN; ILEX PARAGUARIENSIS LEAF; FD&C YELLOW NO. 5; SILICA

84165-013 PRO COLD & HOT Pain Relief Gel Roll-On (Plantar Fasciitis)

ACTIVE INGREDIENT

Menthol 4%

PURPOSE

Topical Analgesic

INDICATIONS AND USAGE

Temporary relieffrom minor aches and pains of sore muscles and joints associated with arthritisbackache, strains and sprains.

WARNINGS

For external use only

do not apply to wounds or damaged skin
do not use with other ointments, creams, sprays,
or liniments.
do not apply to irritated skin
do not bandage or use with heating pad or device

WHEN USING

use only as directed
avoid contact with eyes or mucous membranes
wash hands after use with cool water
store in a cool dry place away from direct sunlight

STOP USE

You experience pain, swelling or blistering; condition worsens, or if symptoms persist for morethan 7 days,or clear up and occur again within a few days.

KEEP OUT OF REACH OF CHILDREN

If swallowed accidentally, get medical help or contact with Poison Control Center immediately.

DOSAGE AND ADMINISTRATION

Adults and Children above 12 years old:Rub a thin film over affected areas not more 4times daily; massage not necessary
Children under age of 12: Consult a doctor

INACTIVE INGREDIENT

Alcohol
Aloe barbadensis leaf extract
Arnica montana flower extract
Boswellia carterii resin extract
Camellia sinensis leaf extract
Carbomer
Camphor
FD&C Blue 1
FD&C Yellow 5
Glycerin
Ilex Paraguariensis Leaf Extract
Isopropyl Myristate
Silica
Triethanolamine
Vitamin E
Water